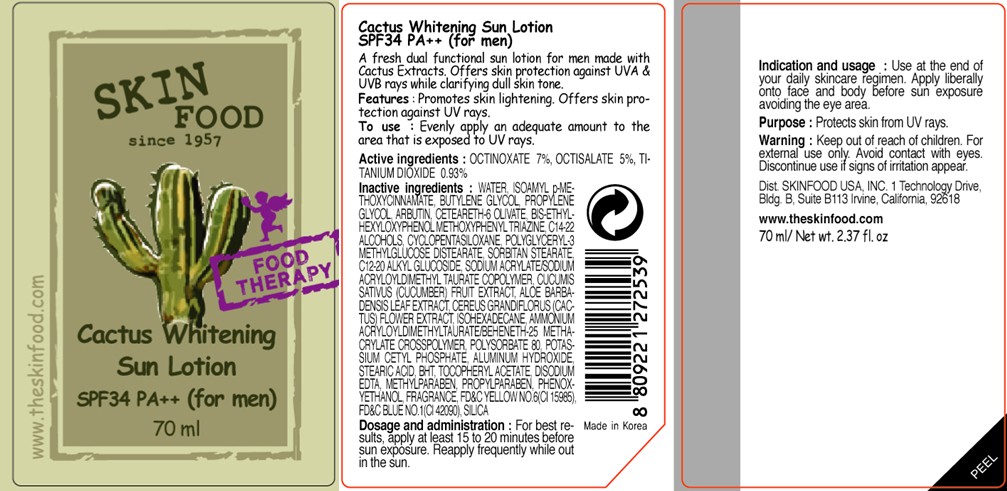 DRUG LABEL: CACTUS WHITENING SUN
NDC: 76214-032 | Form: LOTION
Manufacturer: SKINFOOD CO., LTD.
Category: otc | Type: HUMAN OTC DRUG LABEL
Date: 20111003

ACTIVE INGREDIENTS: OCTINOXATE 4.9 mL/70 mL; OCTISALATE 3.5 mL/70 mL; TITANIUM DIOXIDE 0.65 mL/70 mL
INACTIVE INGREDIENTS: WATER; BUTYLENE GLYCOL; PROPYLENE GLYCOL; ARBUTIN; C14-22 ALCOHOLS; CYCLOMETHICONE 5; SILICON DIOXIDE; SORBITAN MONOSTEARATE; C12-20 ALKYL GLUCOSIDE; PHENOXYETHANOL; CUCUMBER; METHYLPARABEN; ALOE VERA LEAF; ISOHEXADECANE; POLYSORBATE 80; POTASSIUM CETYL PHOSPHATE; PROPYLPARABEN; ALUMINUM HYDROXIDE; STEARIC ACID; BUTYLATED HYDROXYTOLUENE; EDETATE DISODIUM

Drug Facts

ACTIVE INGREDIENT

Active ingredients: OCTINOXATE 7%, OCTISALATE 5%, TITANIUM DIOXIDE 0.93%

Inactive ingredients:
WATER, ISOAMYL p-METHOXYCINNAMATE, BUTYLENE GLYCOL, PROPYLENE GLYCOL, ARBUTIN, CETEARETH-6 OLIVATE, BIS-ETHYLHEXYLOXYPHENOL METHOXYPHENYL TRIAZINE, C14-22 ALCOHOLS, CYCLOPENTASILOXANE, POLYGLYCERYL-3 METHYLGLUCOSE DISTEARATE, SORBITAN STEARATE, C12-20 ALKYL GLUCOSIDE, SODIUM ACRYLATE/SODIUM ACRYLOYLDIMETHYL TAURATE COPOLYMER, CUCUMIS SATIVUS (CUCUMBER) FRUIT EXTRACT, ALOE BARBADENSIS LEAF EXTRACT, CEREUS GRANDIFLORUS (CACTUS) FLOWER EXTRACT, ISOHEXADECANE, AMMONIUM ACRYLOYLDIMETHYLTAURATE/BEHENETH-25 METHACRYLATE CROSSPOLYMER, POLYSORBATE 80, POTASSIUM CETYL PHOSPHATE, ALUMINUM HYDROXIDE, STEARIC ACID, BHT, TOCOPHERYL ACETATE, DISODIUM EDTA, METHYLPARABEN, PROPYLPARABEN, PHENOXYETHANOL, FRAGRANCE, SILICA

Purpose: Protects skin from UV rays.

Warnings:
For external use only.
Avoid contact with eyes.
Discontinue use if signs of irritation appear.

Keep out of reach of children:
Keep out of reach of children.

Indication and usage:
Use at the end of your daily skincare regimen.
Apply liberally onto face and body before sun exposure avoiding the eye area.

Dosage and administration:
For best results, apply at least 15 to 20 minutes before sun exposure.
Reapply frequently while out in the sun.